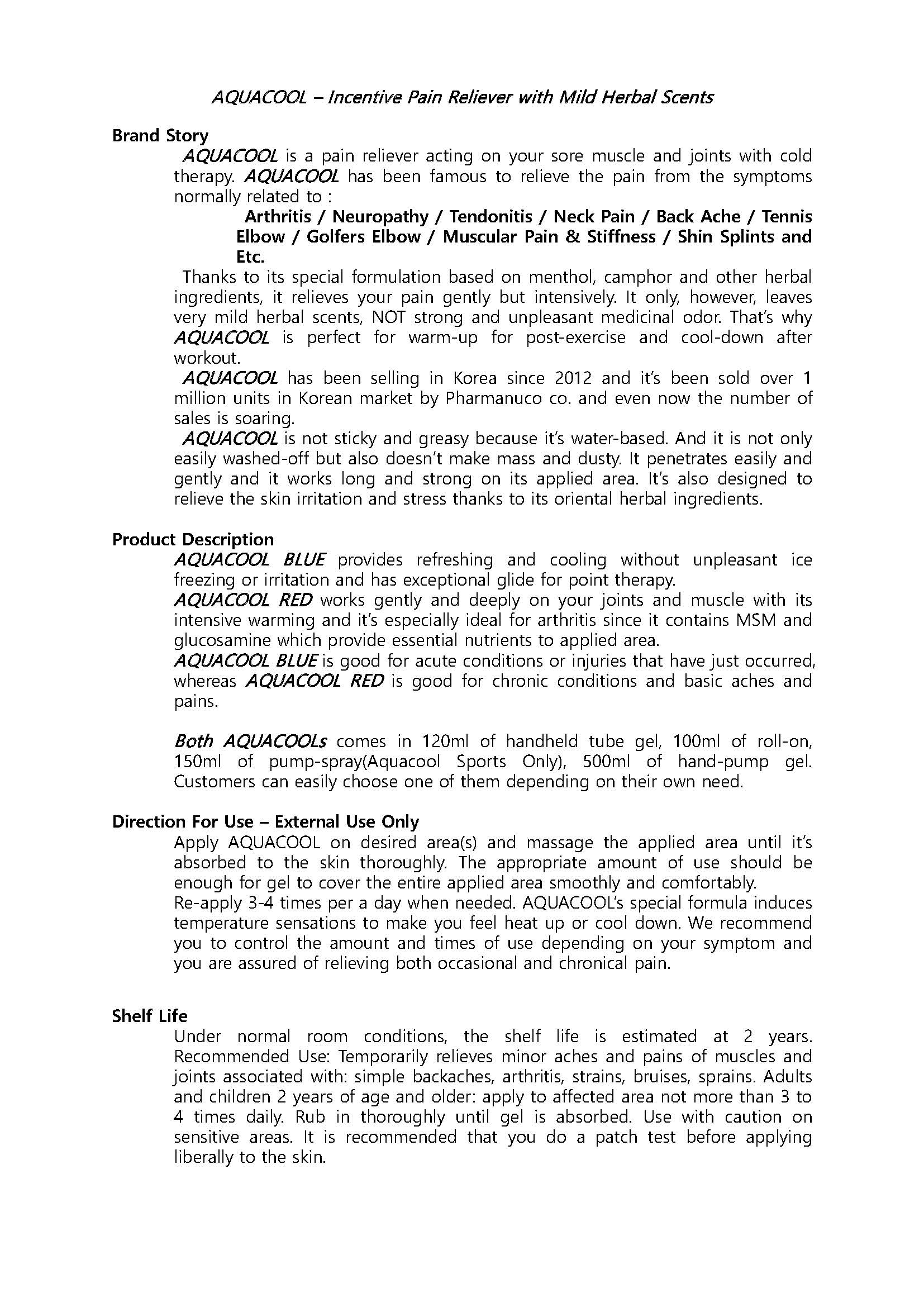 DRUG LABEL: AQUACOOL SHOWER
NDC: 70759-0009 | Form: GEL
Manufacturer: Pharmanuco
Category: otc | Type: HUMAN OTC DRUG LABEL
Date: 20210310

ACTIVE INGREDIENTS: MENTHOL 2.5 g/100 mL
INACTIVE INGREDIENTS: EUCALYPTUS GLOBULUS LEAF; SODIUM LAURETH SULFATE; CAMPHOR, (-)-

Drug Facts

ACTIVE INGREDIENT

MENTHOL

INACTIVE INGREDIENT

Alcohol, Camphor, Eucalyptus Globulus Leaf Oil, Leptospermum Petersonii Oil, Fragrance

PURPOSE

To relieve pain

keep out of reach of the children

INDICATIONS AND USAGE

1. Shake well before use.
2. Hold can more than 20 cm away from treatment area.
3. Apply using a sweeping motion.

DOSAGE AND ADMINISTRATION

for external use only

WARNINGS

1. Under normal room conditions, the shelf life is estimated at 2 years.
2. Recommended Use: Temporarily relieves minor aches and pains of muscles and joints associated with: simple backaches, arthritis, strains, bruises, sprains.
3. Adults and children 2 years of age and older: apply to affected area not more than 3 to 4 times daily.
4. Rub in thoroughly until gel is absorbed.
5. Use with caution on sensitive areas.
6. It is recommended that you do a patch test before applying liberally to the skin.